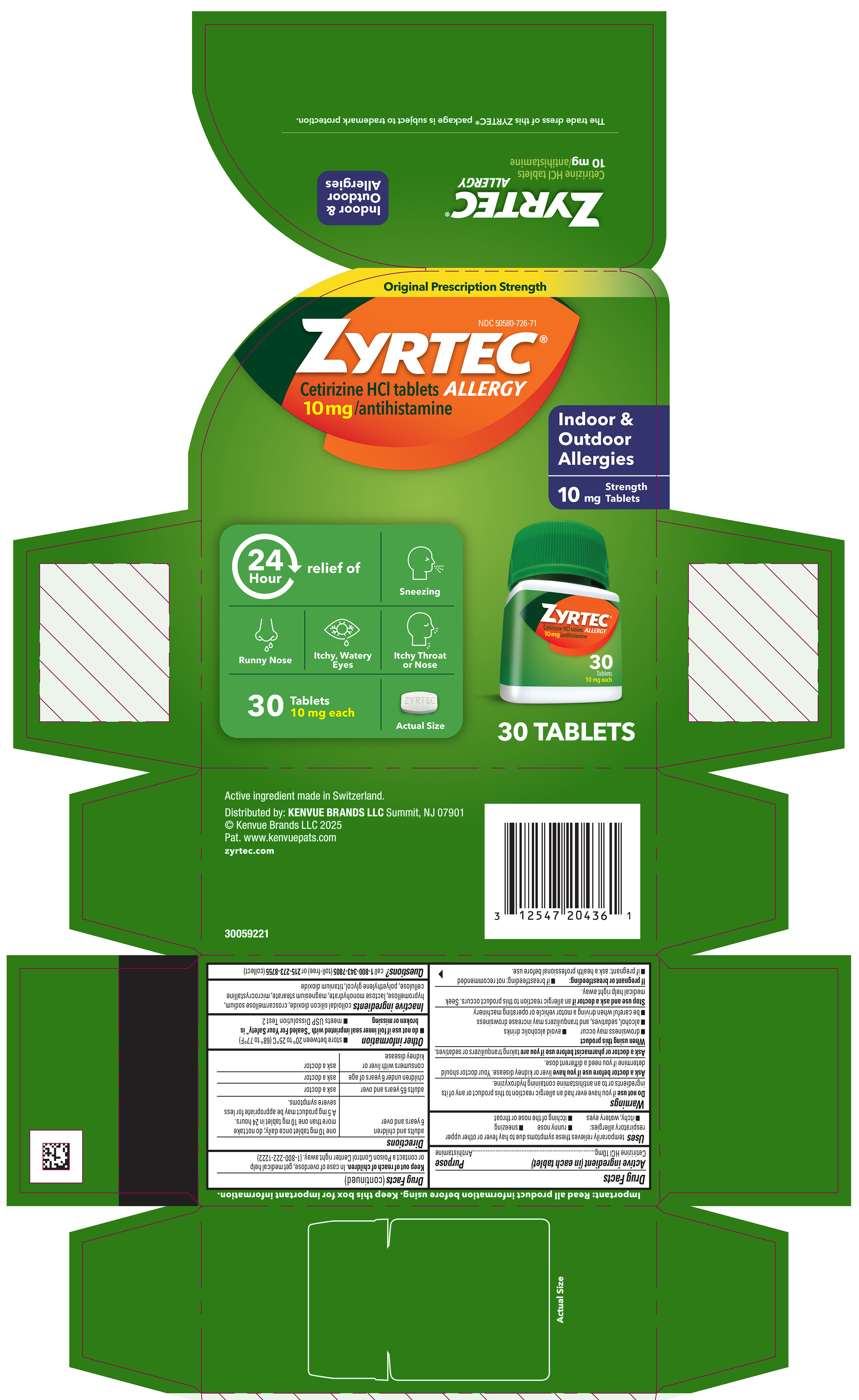 DRUG LABEL: Zyrtec Allergy
NDC: 50580-726 | Form: TABLET, FILM COATED
Manufacturer: Kenvue Brands LLC
Category: otc | Type: HUMAN OTC DRUG LABEL
Date: 20251010

ACTIVE INGREDIENTS: CETIRIZINE HYDROCHLORIDE 10 mg/1 1
INACTIVE INGREDIENTS: SILICON DIOXIDE; CROSCARMELLOSE SODIUM; HYPROMELLOSE, UNSPECIFIED; LACTOSE MONOHYDRATE; MAGNESIUM STEARATE; MICROCRYSTALLINE CELLULOSE; POLYETHYLENE GLYCOL, UNSPECIFIED; TITANIUM DIOXIDE

Zyrtec® Allergy

Drug Facts

Active ingredient (in each tablet)

Cetirizine HCl 10 mg

Purpose

Antihistamine

Uses

temporarily relieves these symptoms due to hay fever or other upper respiratory allergies:

- runny nose
- sneezing
- itchy, watery eyes
- itching of the nose or throat

Warnings

Do not use if you have ever had an allergic reaction to this product or any of its ingredients or to an antihistamine containing hydroxyzine.

Ask a doctor before use if you have liver or kidney disease. Your doctor should determine if you need a different dose.

Ask a doctor or pharmacist before use if you are taking tranquilizers or sedatives.

When using this product

- drowsiness may occur
- avoid alcoholic drinks
- alcohol, sedatives, and tranquilizers may increase drowsiness
- be careful when driving a motor vehicle or operating machinery

Stop use and ask a doctor if an allergic reaction to this product occurs. Seek medical help right away.

If pregnant or breast-feeding

- if breast-feeding: not recommended
- if pregnant: ask a health professional before use.

Keep out of reach of children. In case of overdose, get medical help or contact a Poison Control Center right away. (1-800-222-1222)

Directions

adults and children 6 years and over | one 10 mg tablet once daily; do not take more than one 10 mg tablet in 24 hours. A 5 mg product may be appropriate for less severe symptoms.
adults 65 years and over | ask a doctor
children under 6 years of age | ask a doctor
consumers with liver or kidney disease | ask a doctor

Other information

- store between 20° to 25°C (68° to 77°F)
- do not use if foil inner seal imprinted with “Sealed For Your Safety” is broken or missing
- meets USP Dissolution Test 2

Inactive ingredients

colloidal silicon dioxide, croscarmellose sodium, hypromellose, lactose monohydrate, magnesium stearate, microcrystalline cellulose, polyethylene glycol, titanium dioxide

Questions?

call 1-800-343-7805 (toll-free) or 215-273-8755 (collect)

PRINCIPAL DISPLAY PANEL

Original Prescription Strength

NDC 50580-726-71

ZYRTEC®
ALLERGY

Cetirizine HCl tablets
10 mg /antihistamine

Indoor & Outdoor Allergies

Strength 10mg Tablets
24 hour

Relief of

- Sneezing
- Runny Nose
- Itchy, Watery Eyes
- Itchy Throat or Nose

30 Tablets
10 mg each

Actual Size